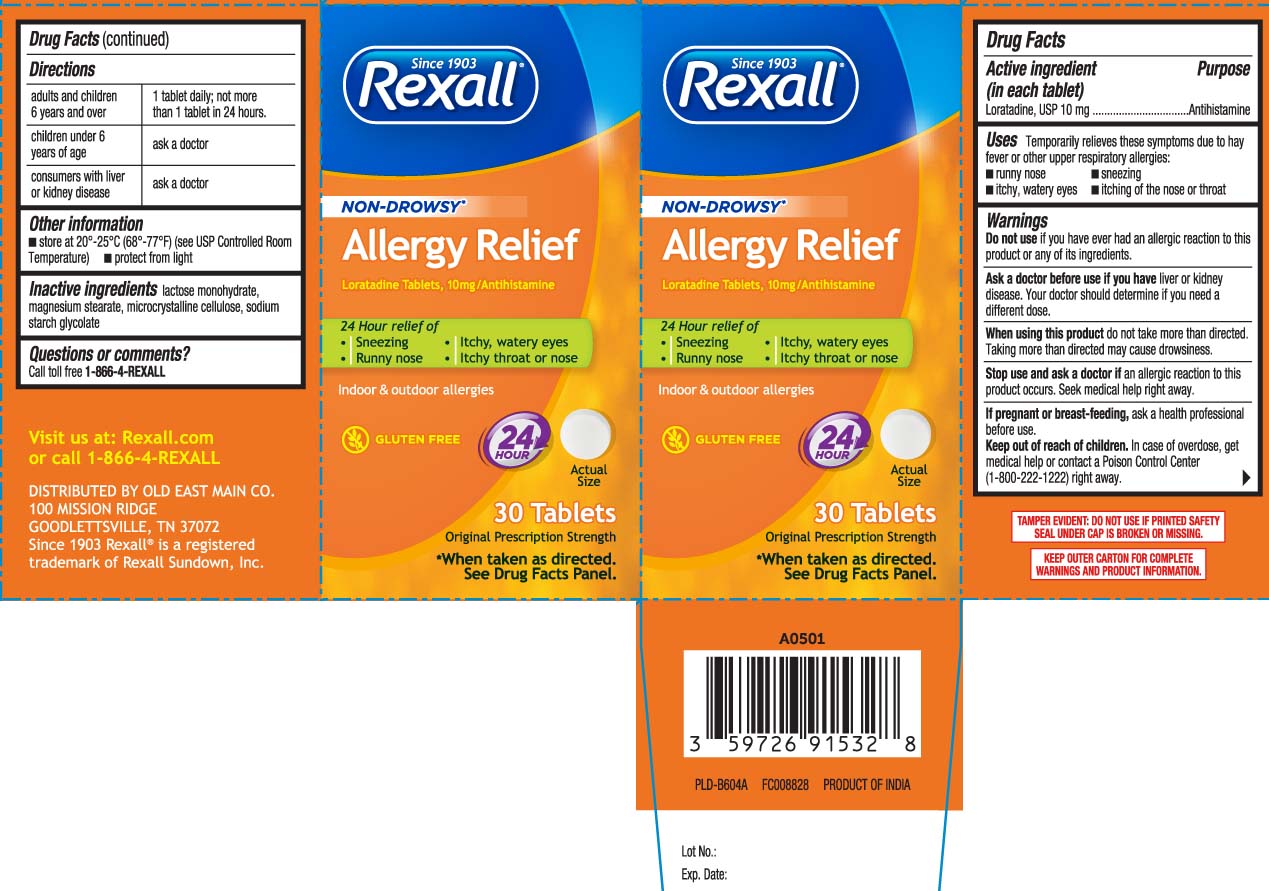 DRUG LABEL: All Day Allergy Relief
NDC: 55910-985 | Form: TABLET
Manufacturer: Dolgencorp, Inc.  (DOLLAR GENERAL & REXALL)
Category: otc | Type: HUMAN OTC DRUG LABEL
Date: 20231129

ACTIVE INGREDIENTS: LORATADINE 10 mg/1 1
INACTIVE INGREDIENTS: LACTOSE MONOHYDRATE; MAGNESIUM STEARATE; MICROCRYSTALLINE CELLULOSE; SODIUM STARCH GLYCOLATE TYPE A

Drug Facts

Active ingredient (in each tablet)

Loratadine, USP 10 mg

Purpose

Antihistamine

Uses

temporarily relieves these symptoms due to hay fever or other upper respiratory allergies:

- runny nose
- sneezing
- itchy, watery eyes
- itching of the nose or throat

Warnings

Do not use

if you have ever had an allergic reaction to this product or any of its ingredients.

Ask a doctor before use if you have

liver or kidney disease. Your doctor should determine if you need a different dose.

When using this product,

do not take more than directed. Taking more than directed may cause drowsiness.

Stop use and ask a doctor if

an allergic reaction to this product occurs. Seek medical help right away

If pregnant or breast-feeding,

ask a health professional before use.

Keep out of reach of children.

In case of overdose, get medical help or contact a Poison Control Center (1-800-222-1222) right away.

Directions

adults and children 6 years and over | 1 tablet daily; not more than 1 tablet in 24 hours
children under 6 years of age | ask a doctor
consumers with liver or kidney disease | ask a doctor

Other information

- store at 20º-25ºC (68º-77ºF) (see USP Controlled Room Temperature)
- protect from light

Inactive ingredient

lactose monohydrate, magnesium stearate, microcrystalline cellulose, sodium starch glycolate

Questions or comments?

Call toll free 1-866-4-REXALL

Principal Display Panel

NON-DROWSY*

Allergy Relief

Loratadine Tablets, 10 mg/Antihistamine

24-hour relief of

- Sneezing
- Runny nose
- Itchy, watery eyes
- Itchy throat or nose

Indoor & Outdoor allergies

GLUTEN FREE

Original Prescription Strength

*When taken as directed, see drug facts panel.

Tablets

TAMPER EVIDENT: DO NOT USE IF PRINTED SAFETY SEAL UNDER CAP IS BROKEN OR MISSING

KEEP OUTER CARTON FOR COMPLETE WARNINGS AND PRODUCT INFORMATION

DISTRIBUTED BY

OLD EAST MAIN CO.

100 MISSION RIDGE

GOODLETTSVILLE, TN 37072

Package Label

REXALL Non-Drowsy Allergy Relief